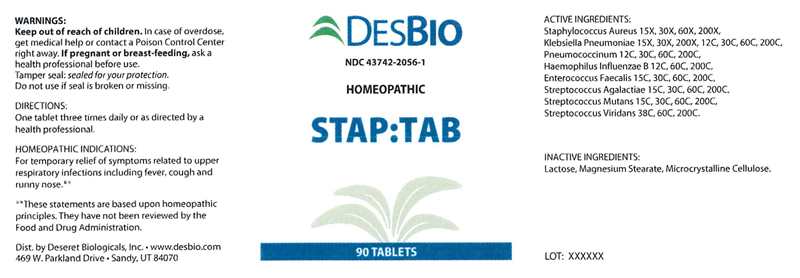 DRUG LABEL: STAP TAB
NDC: 43742-2056 | Form: TABLET
Manufacturer: Deseret Biologicals, Inc.
Category: homeopathic | Type: HUMAN OTC DRUG LABEL
Date: 20240117

ACTIVE INGREDIENTS: STAPHYLOCOCCUS AUREUS 15 [hp_X]/1 1; KLEBSIELLA PNEUMONIAE 15 [hp_X]/1 1; STREPTOCOCCUS PNEUMONIAE 12 [hp_C]/1 1; HAEMOPHILUS INFLUENZAE TYPE B 12 [hp_C]/1 1; ENTEROCOCCUS FAECALIS 15 [hp_C]/1 1; STREPTOCOCCUS AGALACTIAE 15 [hp_C]/1 1; STREPTOCOCCUS MUTANS 15 [hp_C]/1 1; STREPTOCOCCUS VIRIDANS GROUP 38 [hp_C]/1 1
INACTIVE INGREDIENTS: LACTOSE MONOHYDRATE; MAGNESIUM STEARATE; CELLULOSE, MICROCRYSTALLINE

DRUG FACTS:

ACTIVE INGREDIENTS:

Staphylococcus Aureus 15X, 30X, 60X, 200X, Klebsiella Pneumoniae 15X, 30X, 200X, 12C, 30C, 60C, 200C, Pneumococcinum 12C, 30C, 60C, 200C, Haemophilus Influenzae B 12C, 60C, 200C, Enterococcus Faecalis 15C, 30C, 60C, 200C, Streptococcus Agalactiae 15C, 30C, 60C, 200C, Streptococcus Mutans 15C, 30C, 60C, 200C, Streptococcus Viridans 38C, 60C, 200C.

HOMEOPATHIC INDICATIONS:

For temporary relief of symptoms related to upper respiratory infections including fever, cough and runny nose.**

**These statements are based upon homeopathic principles. They have not been reviewed by the Food and Drug Administration.

WARNINGS:

Keep out of reach of children. In case of overdose, get medical help or contact a Poison Control Center right away.

If pregnant or breast-feeding, ask a health professional before use.

Tamper seal: Sealed for your protection.

Do not use if seal is broken or missing.

Keep out of reach of children. In case of overdose, get medical help or contact a Poison Control Center right away.

DIRECTIONS:

One tablet three times daily or as directed by a health professional.

HOMEOPATHIC INDICATIONS:

For temporary relief of symptoms related to upper respiratory infections including fever, cough and runny nose.**

**These statements are based upon homeopathic principles. They have not been reviewed by the Food and Drug Administration.

INACTIVE INGREDIENTS:

Lactose, Magnesium Stearate, Microcrystalline Cellulose.

QUESTIONS:

Dist. by Deseret Biologicals, Inc. • www.desbio.com
469 W. Parkland Drive • Sandy, UT 84070

PACKAGE LABEL DISPLAY:

DESBIO

NDC 43742-2056-1

HOMEOPATHIC

STAP:TAB

90 TABLETS